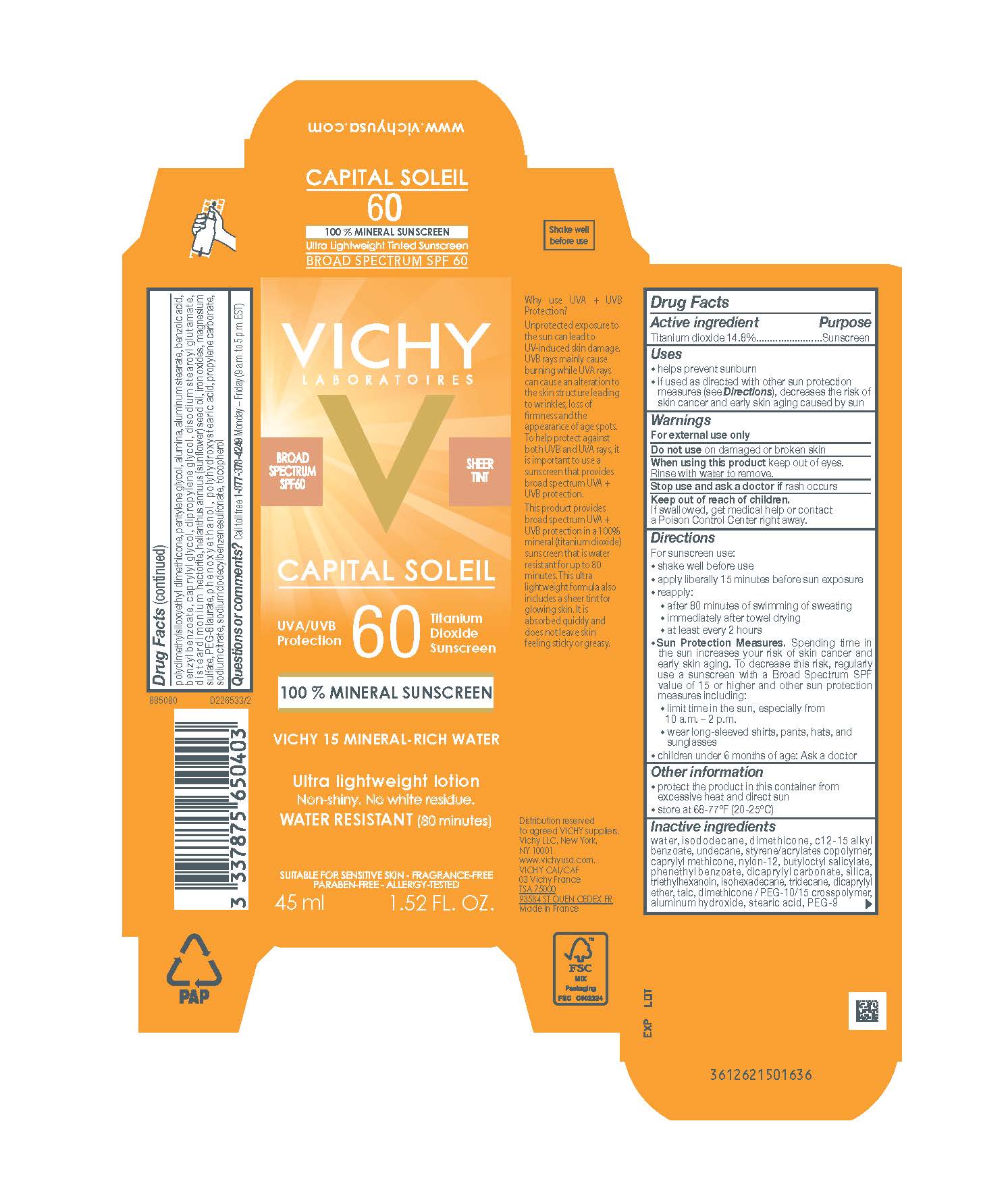 DRUG LABEL: Vichy Laboratoires Capital Soleil 60 Mineral Broad Spectrum SPF 60 Water Resistant 80 Minutes Sheer Tint Ultra Lightweight Sunscreen
NDC: 69625-651 | Form: LOTION
Manufacturer: Cosmetique Active Production
Category: otc | Type: HUMAN OTC DRUG LABEL
Date: 20231211

ACTIVE INGREDIENTS: TITANIUM DIOXIDE 148 mg/1 mL
INACTIVE INGREDIENTS: WATER; ISODODECANE; DIMETHICONE; ALKYL (C12-15) BENZOATE; UNDECANE; STYRENE/ACRYLAMIDE COPOLYMER (500000 MW); CAPRYLYL TRISILOXANE; NYLON-12; BUTYLOCTYL SALICYLATE; PHENETHYL BENZOATE; DICAPRYLYL CARBONATE; SILICON DIOXIDE; TRIETHYLHEXANOIN; ISOHEXADECANE; TRIDECANE; DICAPRYLYL ETHER; TALC; DIMETHICONE/PEG-10/15 CROSSPOLYMER; ALUMINUM HYDROXIDE; STEARIC ACID; PEG-9 POLYDIMETHYLSILOXYETHYL DIMETHICONE; PENTYLENE GLYCOL; ALUMINUM OXIDE; ALUMINUM STEARATE; BENZOIC ACID; BENZYL BENZOATE; CAPRYLYL GLYCOL; FERRIC OXIDE RED; DIPROPYLENE GLYCOL; DISODIUM STEAROYL GLUTAMATE; DISTEARDIMONIUM HECTORITE; MAGNESIUM SULFATE, UNSPECIFIED FORM; PEG-8 LAURATE; PHENOXYETHANOL; POLYHYDROXYSTEARIC ACID (2300 MW); PROPYLENE CARBONATE; SODIUM CITRATE; SODIUM DODECYLBENZENESULFONATE; TOCOPHEROL

Drug Facts

Active ingredients

Titanium dioxide 14.8%

Purpose

Sunscreen

Uses

- helps prevent sunburn
- if used as directed with other sun protection measures (see Directions), decreases the risk of skin cancer and early skin aging caused by the sun

Warnings

For external use only

Do not use

on damaged or broken skin

When using this product

keep out of eyes. Rinse with water to remove.

Stop use and ask a doctor if

rash occurs

Keep out of reach of children.

If swallowed, get medical help or contact a Poison Control Center right away.

Directions

For sunscreen use:

- shake well before use

● apply liberally 15 minutes before sun exposure

● reapply:

● after 80 minutes of swimming or sweating

● immediately after towel drying

● at least every 2 hours

● Sun Protection Measures. Spending time in the sun increases your risk of skin cancer and early skin aging. To decrease this risk, regularly use a sunscreen with a Broad Spectrum SPF value of 15 or higher and other sun protection measures including:

● limit time in the sun, especially from 10 a.m. – 2 p.m.

● wear long-sleeved shirts, pants, hats, and sunglasses

● children under 6 months of age: Ask a doctor

Other information

- protect the product in this container from excessive heat and direct sun
- store at 68 – 77° F (20 – 25°C)

Inactive ingredients

water, isododecane, dimethicone, c12-15 alkyl benzoate, undecane, styrene/acrylates copolymer, caprylyl methicone, nylon-12, butyloctyl salicylate, phenethyl benzoate, dicaprylyl carbonate, silica, triethylhexanoin, isohexadecane, tridecane, dicaprylyl ether, talc, dimethicone/PEG-10/15 crosspolymer, aluminum hydroxide, stearic acid, PEG-9 polydimethylsiloxyethyl dimethicone, pentylene glycol, alumina, aluminum stearate, benzoic acid, benzyl benzoate, caprylyl glycol, iron oxides, dipropylene glycol, disodium stearoyl glutamate, disteardimonium hectorite, helianthus annuus seed oil/sunflower seed oil, magnesium sulfate, PEG-8 laurate, phenoxyethanol, polyhydroxystearic acid, propylene carbonate, sodium citrate, sodium dodecylbenzenesulfonate, tocopherol

Questions or comments?

Call toll free 1-877-378-4249

Monday - Friday (9 a.m. to 5 p.m. EST)